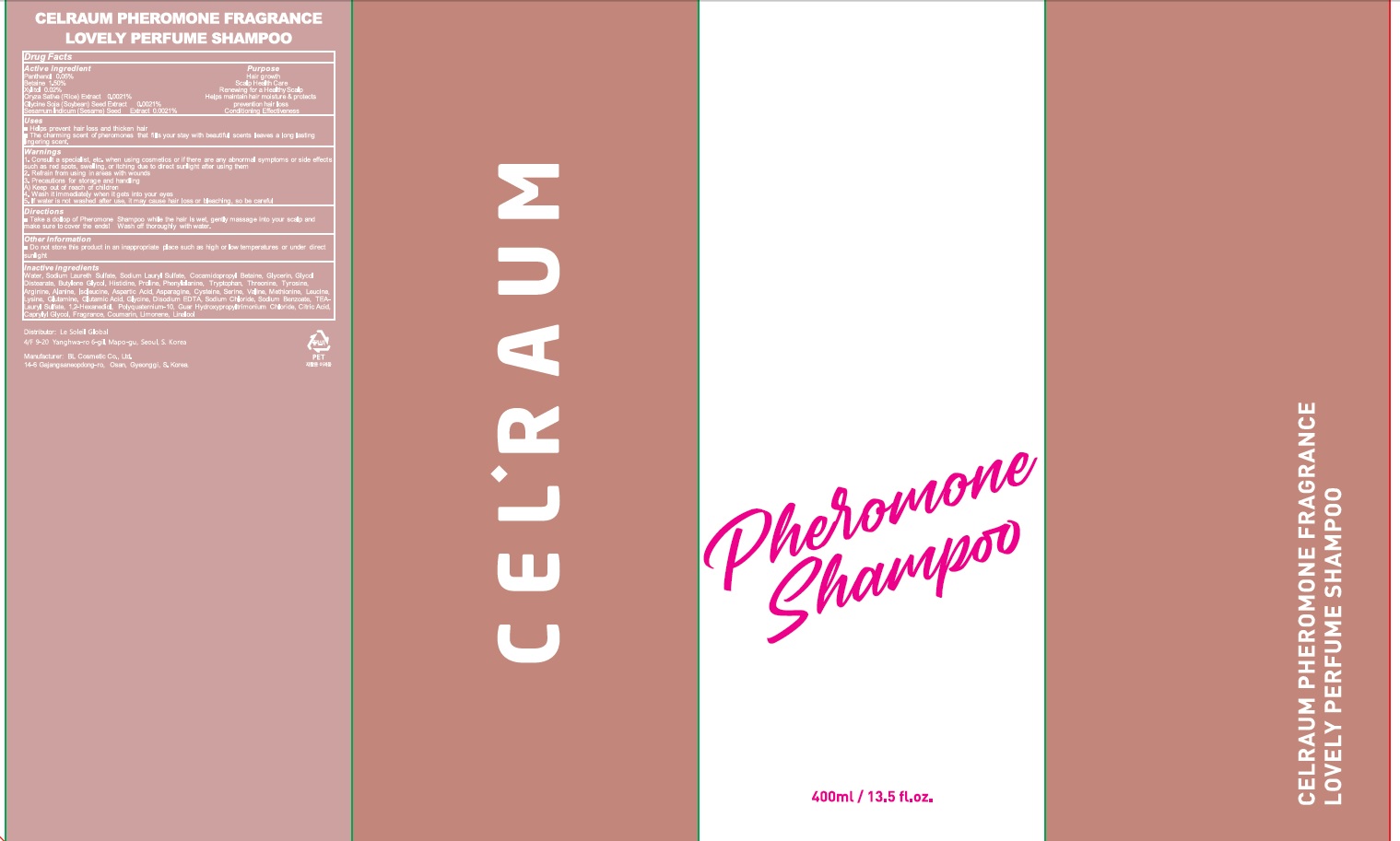 DRUG LABEL: CELRAUM PHEROMONE FRAGRANCE LOVELY PERFUME
NDC: 75368-040 | Form: SHAMPOO
Manufacturer: Le Soleil Global
Category: otc | Type: HUMAN OTC DRUG LABEL
Date: 20221013

ACTIVE INGREDIENTS: Panthenol 0.05 g/100 mL; Betaine 1.50 g/100 mL; Xylitol 0.02 g/100 mL; RICE GERM 0.0021 g/100 mL; SOYBEAN 0.0021 g/100 mL; SESAME SEED 0.0021 g/100 mL
INACTIVE INGREDIENTS: WATER; SODIUM LAURETH-3 SULFATE

ACTIVE INGREDIENT

Panthenol 0.05%
Betaine 1.50%
Xylitol 0.02%
Oryza Sativa (Rice) Extract 0.0021%
Glycine Soja (Soybean) Seed Extract 0.0021%
Sesamum Indicum (Sesame) Seed Extract 0.0021%

INACTIVE INGREDIENT

Water, Sodium Laureth Sulfate, Sodium Lauryl Sulfate, Cocamidopropyl Betaine, Glycerin, Glycol Distearate, Butylene Glycol, Histidine, Proline, Phenylalanine, Tryptophan, Threonine, Tyrosine, Arginine, Alanine, Isoleucine, Aspartic Acid, Asparagine, Cysteine, Serine, Valine, Methionine, Leucine, Lysine, Glutamine, Glutamic Acid, Glycine, Disodium EDTA, Sodium Chloride, Sodium Benzoate, TEA-Lauryl Sulfate, 1,2-Hexanediol, Polyquaternium-10, Guar Hydroxypropyltrimonium Chloride, Citric Acid, Caprylyl Glycol, Fragrance, Coumarin, Limonene, Linalool

PURPOSE

Hair growth
Scalp Health Care
Renewing for a Healthy Scalp
Helps maintain hair moisture & protects
Skin/Scalp follicle protection
Anti-Cancer Efficacy

WARNINGS

1. Consult a specialist, etc. when using cosmetics or if there are any abnormal symptoms or side effects such as red spots, swelling, or itching due to direct sunlight after using them
2. Refrain from using in areas with wounds
3. Precautions for storage and handling
A) Keep out of reach of children
4. Wash it immediately when it gets into your eyes
5. If water is not washed after use, it may cause hair loss or bleaching, so be careful

KEEP OUT OF REACH OF CHILDREN

Uses

■ Helps prevent hair loss and thicken hair
■ The charming scent of pheromones that fills your stay with beautiful scents leaves a long lasting lingering scent.

Directions

■ Take a dallop of Pheromone Shampoo while the hair is wet, gently massage into your scalp and make sure to cover the ends! Wash off thoroughly with water.

Other information

■ Do not store this product in an inappropriate place such as high or low temperatures or under direct sun light